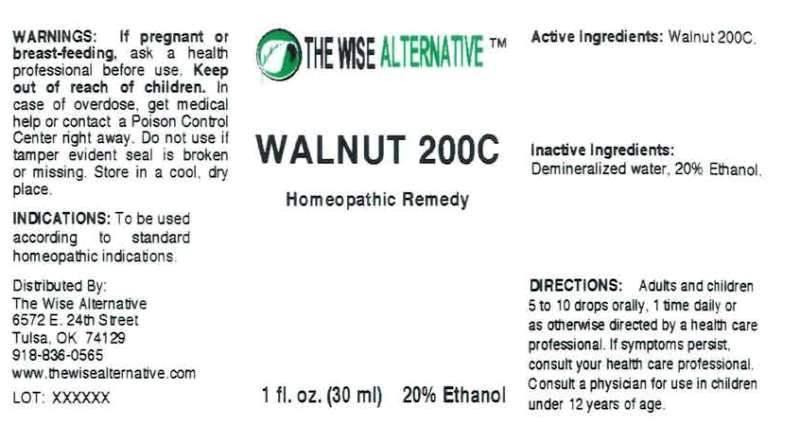 DRUG LABEL: Walnut
NDC: 51096-0004 | Form: LIQUID
Manufacturer: The Wise Alternative
Category: homeopathic | Type: HUMAN OTC DRUG LABEL
Date: 20130913

ACTIVE INGREDIENTS: ENGLISH WALNUT 200 [hp_C]/1 mL
INACTIVE INGREDIENTS: WATER; ALCOHOL

DRUG FACTS:

ACTIVE INGREDIENTS:

Walnut 200C

INDICATIONS:

To be used according to standard homeopathic indications.

WARNINGS:

If pregnant or breast-feeding, ask a health professional before use.

Keep out of reach of children. In case of overdose, get medical help or contact a Poison Control Center right away.

Do not use if tamper evident seal is broken or missing.

Store in a cool, dry place.

Keep out of reach of children. In case of overdose, get medical help or contact a Poison Control Center right away.

DIRECTIONS:

Adults and children 5 to 10 drops orally. 1 time daily or as otherwise directed by a health care professional. If symptoms persist, consult your health care professional. Consult a physician for use in children under 12 years of age.

INDICATIONS:

To be used according to standard homeopathic indications.

INACTIVE INGREDIENTS:

Demineralized Water, 20% Ethanol

QUESTIONS:

Distributed By:

The Wise Alternative

6572 E. 24th Street

Tulsa, OK 74129

918-836-0565

www.thewisealternative.com

PACKAGE DISPLAY LABEL:

THE WISE ALTERNATIVE

WALNUT 200C

Homeopathic Remedy

1 fl. oz. (30 ml) 20% Ethanol